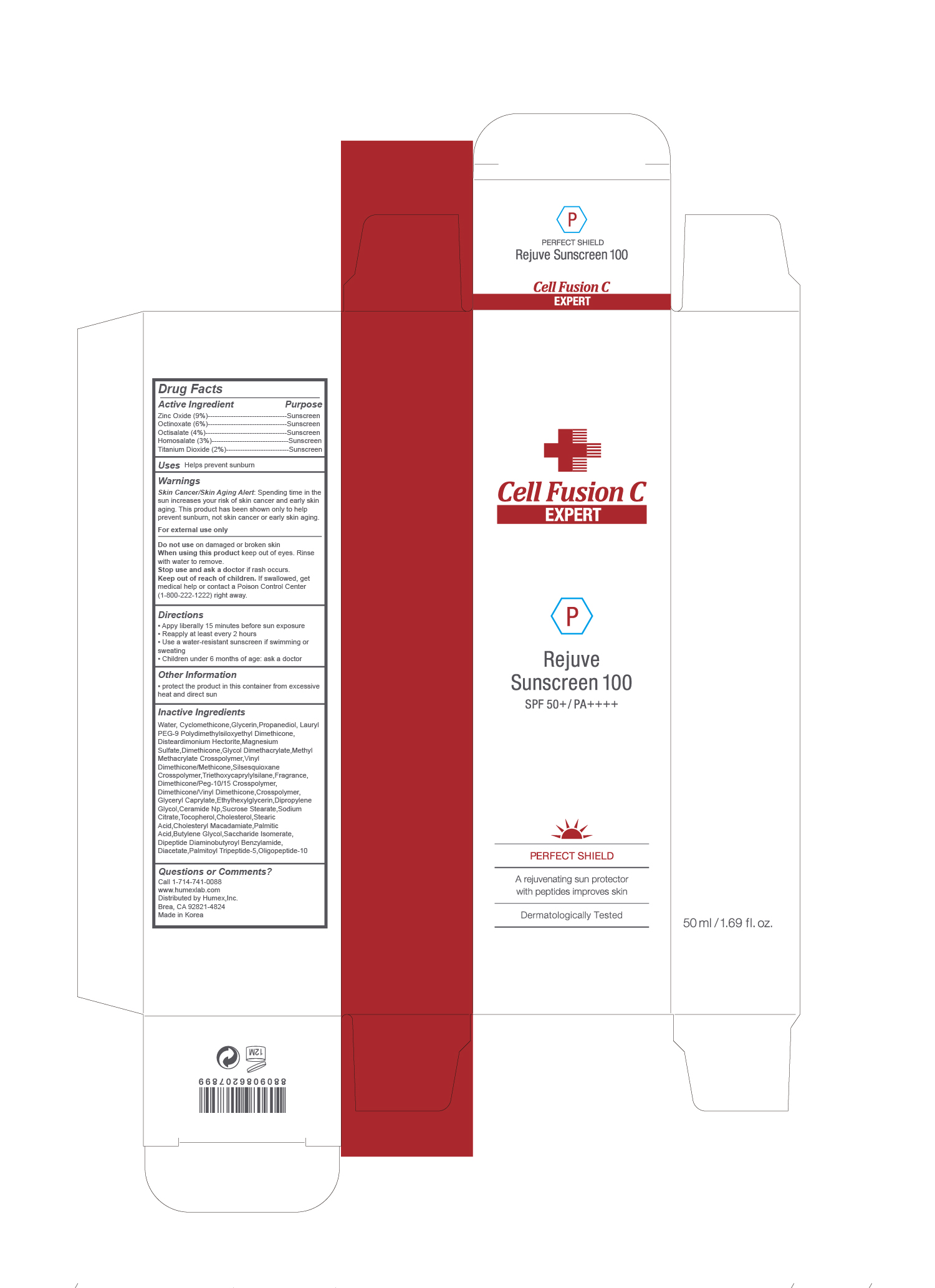 DRUG LABEL: Rejuve Sunscreen 100
NDC: 76344-8005 | Form: CREAM
Manufacturer: HUMEX,INC.
Category: otc | Type: HUMAN OTC DRUG LABEL
Date: 20230110

ACTIVE INGREDIENTS: ZINC OXIDE 9 g/100 mL; TITANIUM DIOXIDE 2 g/100 mL; OCTINOXATE 6 g/100 mL; OCTISALATE 4 g/100 mL; HOMOSALATE 3 g/100 mL
INACTIVE INGREDIENTS: DIMETHICONE/VINYL DIMETHICONE CROSSPOLYMER (SOFT PARTICLE) 0.12 mL/100 mL; BUTYLENE GLYCOL 0.01 mL/100 mL; SACCHARIDE ISOMERATE 0.01 mL/100 mL; OLIGOPEPTIDE-10 0.01 mL/100 mL; GLYCERIN 3 mL/100 mL; PROPANEDIOL 3 mL/100 mL; SUCROSE STEARATE 0.01 mL/100 mL; SODIUM CITRATE 0.01 mL/100 mL; TOCOPHEROL 0.01 mL/100 mL; STEARIC ACID 0.01 mL/100 mL; PALMITIC ACID 0.01 mL/100 mL; GLYCERYL CAPRYLATE 0.1 mL/100 mL; LAURYL PEG-9 POLYDIMETHYLSILOXYETHYL DIMETHICONE 2.49 mL/100 mL; DISTEARDIMONIUM HECTORITE 0.8 mL/100 mL; MAGNESIUM SULFATE, UNSPECIFIED 0.8 mL/100 mL; DIMETHICONE 0.52 mL/100 mL; GLYCOL DIMETHACRYLATE 0.5 mL/100 mL; 1,2-HEXANEDIOL 0.5 mL/100 mL; VINYL DIMETHICONE/METHICONE SILSESQUIOXANE CROSSPOLYMER 0.5 mL/100 mL; TRIETHOXYCAPRYLYLSILANE 0.46 mL/100 mL; ETHYLHEXYLGLYCERIN 0.04 mL/100 mL; DIPROPYLENE GLYCOL 0.01 mL/100 mL; CERAMIDE NP 0.01 mL/100 mL; PALMITOYL TRIPEPTIDE-5 0.01 mL/100 mL; CHOLESTEROL 0.01 mL/100 mL; CHOLESTERYL MACADAMIATE 0.01 mL/100 mL; DIPEPTIDE DIAMINOBUTYROYL BENZYLAMIDE DIACETATE 0.01 mL/100 mL; CYCLOMETHICONE 19.08 mL/100 mL

Uses

Helps prevent sunburn

Warnings

Skin Cancer/Skin Aging Alert: Spending time in the sun increases your risk of skin cancer and early skin aging. This product has been shown only to help prevent sunburn, not skin cancer or early skin aging.

For external use only

Do not use on damaged or broken skin
When using this product keep out of eyes. Rinse with water to remove.
Stop use and ask a doctor if rash occurs.
Keep out of reach of children. If swallowed, get medical help or contact a Poison Control Center (1-800-222-1222) right away.

Directions

▪ Appy liberally 15 minutes before sun exposure
▪ Reapply at least every 2 hours
▪ Use a water-resistant sunscreen if swimming or sweating
▪ Children under 6 months of age: ask a doctor

Other Information

▪ protect the product in this container from excessive heat and direct sun

Inactive Ingredients

Water, Cyclomethicone,Glycerin,Propanediol, Lauryl PEG-9 Polydimethylsiloxyethyl Dimethicone, Disteardimonium Hectorite,Magnesium Sulfate,Dimethicone,Glycol Dimethacrylate,Methyl Methacrylate Crosspolymer,Vinyl Dimethicone/Methicone,Silsesquioxane Crosspolymer,Triethoxycaprylylsilane,Fragrance,
Dimethicone/Peg-10/15 Crosspolymer,
Dimethicone/Vinyl Dimethicone,Crosspolymer,
Glyceryl Caprylate,Ethylhexylglycerin,Dipropylene Glycol,Ceramide Np,Sucrose Stearate,Sodium Citrate,Tocopherol,Cholesterol,Stearic Acid,Cholesteryl Macadamiate,Palmitic Acid,Butylene Glycol,Saccharide Isomerate,
Dipeptide Diaminobutyroyl Benzylamide,
Diacetate,Palmitoyl Tripeptide-5,Oligopeptide-10